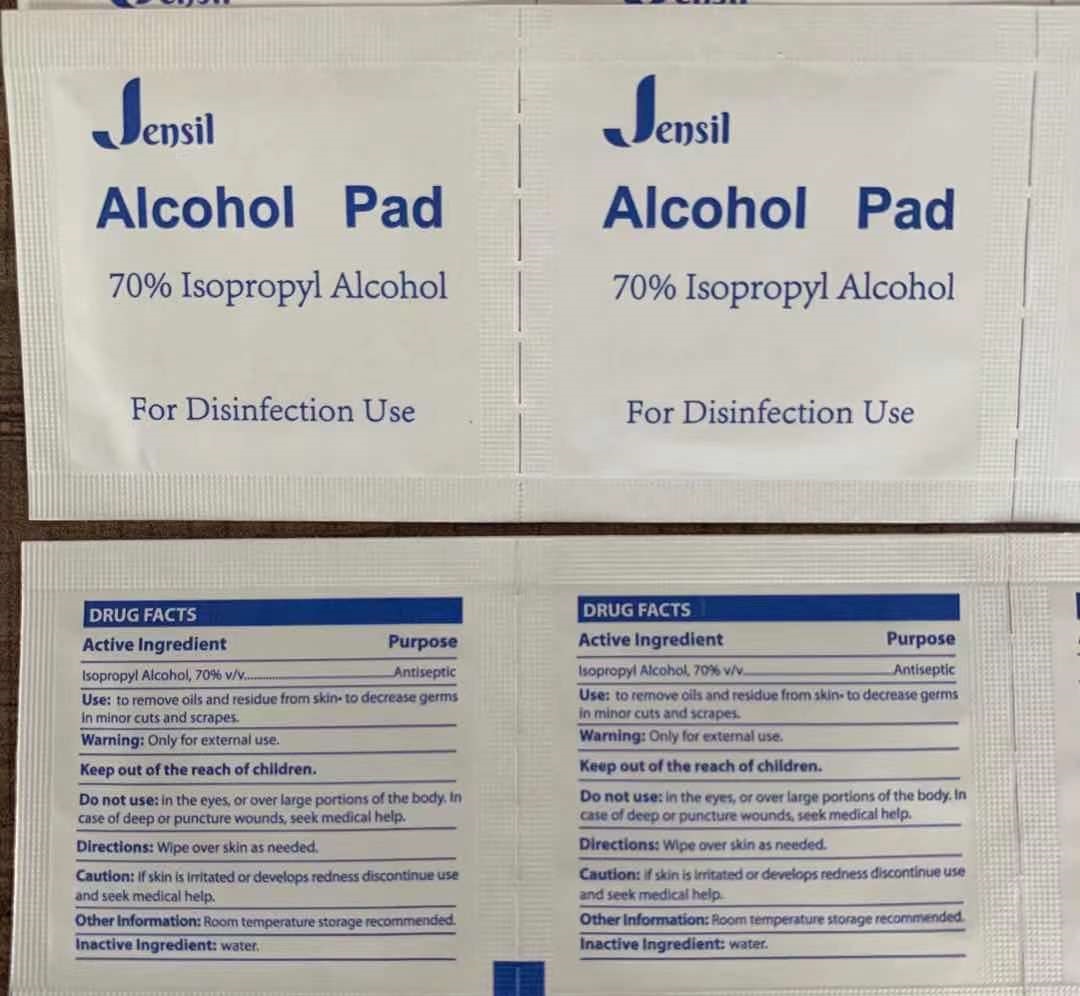 DRUG LABEL: Jensil Alcohol Pad
NDC: 69139-212 | Form: SWAB
Manufacturer: YIWU HAODING MEDICAL CO.,LTD
Category: otc | Type: HUMAN OTC DRUG LABEL
Date: 20230303

ACTIVE INGREDIENTS: ALCOHOL 70 g/100 g
INACTIVE INGREDIENTS: WATER

DRUG FACTS

Active Ingredient

Isopropyl Alcohol 70%

Purpose

Antiseptic

Uses:

To remove oils and residue from skin.

To Decrease germs in minor cuts and scrapes.

Discard after single use.

Other Information: Room temperature storage recommended.

WARNINGS

For external use only.

Flammable, keep away from heat and flame.

Do not use: in the eyes, or over large portions of the body. In case of deep or puncture wounds, seek medical help.

STOP USE

Caustion: If skin is irritated or develops redness discontinue use and seek medical help.

Keep out of reach of children.

If ingested, do not induce vomiting. Get medical help or contact a Poison Control Center immediately.

Inactive Ingredients:

water